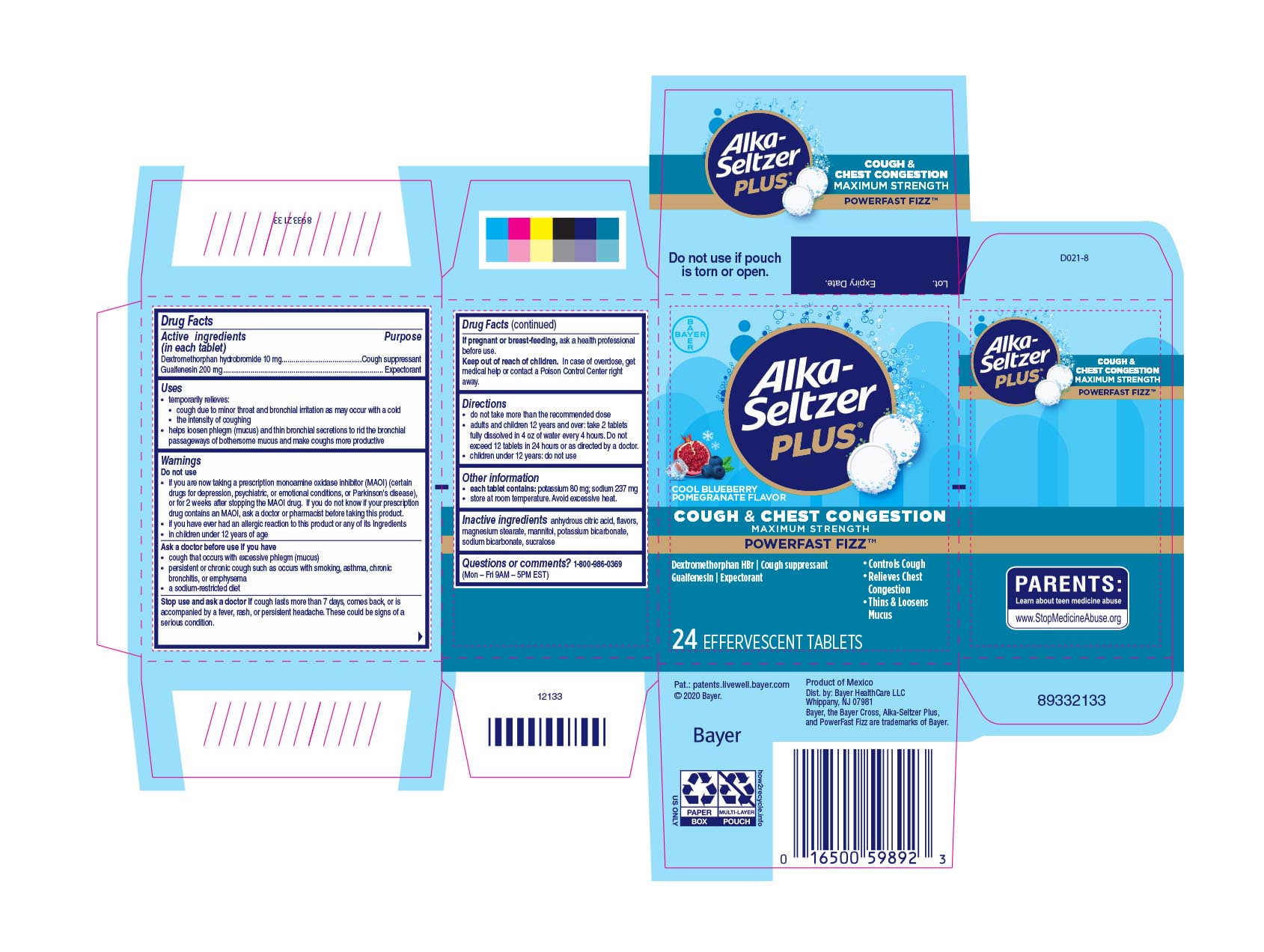 DRUG LABEL: Alka Seltzer Plus Maximum Strength Cough Chest Congestion  PowerFast Fizz
NDC: 0280-0089 | Form: TABLET, EFFERVESCENT
Manufacturer: Bayer Healthcare LLC.
Category: otc | Type: HUMAN OTC DRUG LABEL
Date: 20251204

ACTIVE INGREDIENTS: DEXTROMETHORPHAN HYDROBROMIDE 10 mg/1 1; GUAIFENESIN 200 mg/1 1
INACTIVE INGREDIENTS: CALCIUM SILICATE; DIMETHICONE; ANHYDROUS CITRIC ACID; POVIDONE; POTASSIUM BICARBONATE; SUCRALOSE; SODIUM BICARBONATE; MANNITOL

Alka-Seltzer Plus Severe Cold & Cough PowerFast Fizz Effervescent Tablets

Drug Facts

Active ingredients (in each tablet) Purposes

Dextromethorphan hydrobromide 10 mg………….…Cough suppressant

Guaifenesin 200 mg.......…………….….................................Expectorant

Uses

- temporarily relieves:
- cough due to minor throat and bronchial irritation as may occur with a cold
- the intensity of coughing
- helps loosen phlegm (mucus) and thin bronchial secretions to rid the bronchial passageways of bothersome mucus and make coughs more productive

Warnings

Do not use

● if you are now taking a prescription monoamine oxidase inhibitor (MAOI) (certain drugs for depression, psychiatric, or emotional conditions, or Parkinson's disease), or for 2 weeks after stopping the MAOI drug. If you do not know if your prescription drug contains an MAOI, ask a doctor or pharmacist before taking this product.

● if you have ever had an allergic reaction to this product or any of its Ingredients

● in children under 12 years of age

Ask a doctor before use if you have

● cough that occurs with excessive phlegm (mucus) ● persistent or chronic cough such as occurs with smoking, asthma, chronic bronchitis, or emphysema ● a sodium-restricted diet

Stop use and ask a doctor if cough lasts more than 7 days, comes back, or is accompanied by a fever, rash, or persistent headache. These could be signs of a serious condition.

If pregnant or breast-feeding, ask a health professional before use.

Keep out of reach of children. In case of overdose, get medical help or contact a Poison Control Center right away

Directions

- do not take more than the recommended dose
- adults and children 12 years and over: take 2 tablets fully dissolved in 4 oz of water every 4 hours. Do not exceed 12 tablets in 24 hours or as directed by a doctor.
- children under 12 years: do not use

Other information
● each tablet contains: potassium 80 mg; sodium 237 mg

● store at room temperature. Avoid excessive heat.

INACTIVE INGREDIENT

anhydrous citric acid, flavors, magnesium stearate, mannitol, potassium bicarbonate, sodium bicarbonate, sucralose

Questions or comments? 1-800-986-0369 (Mon - Fri 9AM - 5PM EST)

Carton 24 count

Alka Seltzer Plus Maximum Strength Cough & Chest Congestion

POWERFAST FIZZ™

Dextromethorphan HBr / Cough Suppressant

Guaifenesin/Expectorant

24 EFFERVESCENT TABLETS